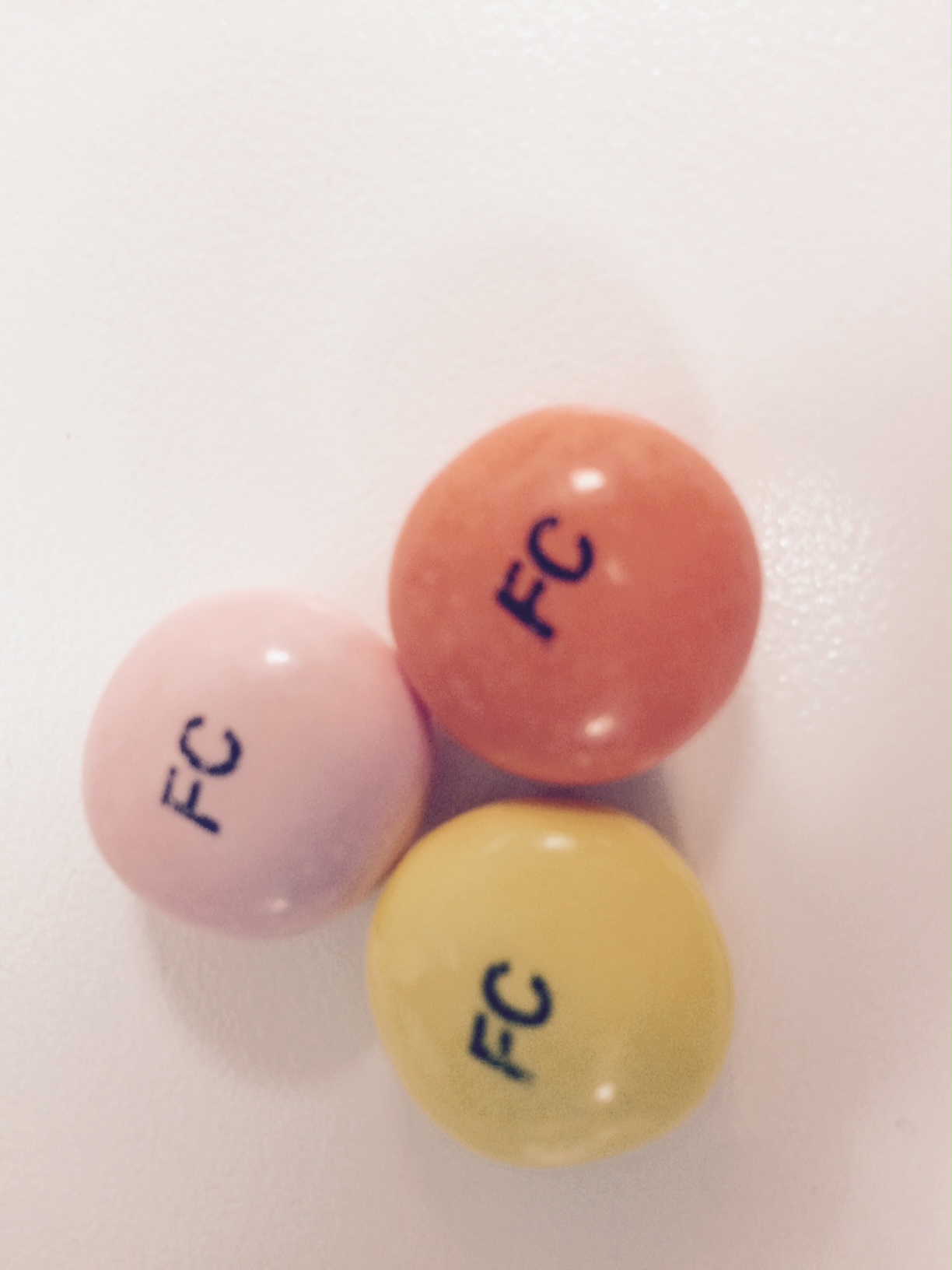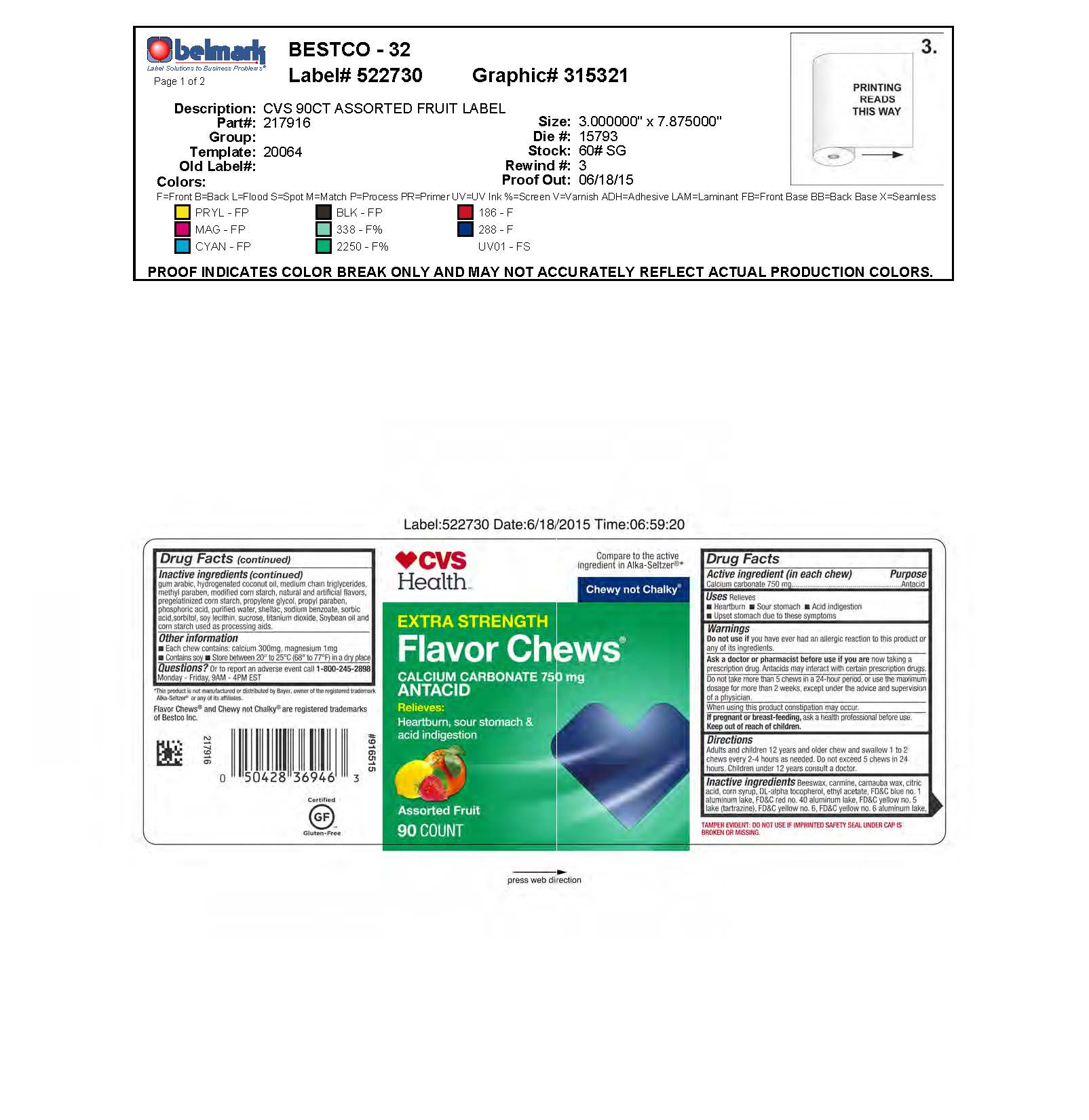 DRUG LABEL: Assorted Fruit Antacid Flavor Chews
NDC: 59779-748 | Form: TABLET, CHEWABLE
Manufacturer: CVS Pharmacy
Category: otc | Type: HUMAN OTC DRUG LABEL
Date: 20251207

ACTIVE INGREDIENTS: CALCIUM CARBONATE 750 mg/1 1
INACTIVE INGREDIENTS: SUCROSE

Calcium Carbonate 750 mg

Active ingredient (in each chew)

Calcium carbonate 750 mg

Purpose

Antacid

INDICATIONS AND USAGE

Uses: Relieves

Heartburn

Sour stomach

Acid indigestion

Upset stomach due to these symptoms

Warnings

Do not use if you have ever had a allergic reaction to this product or any of its ingredients.

Ask a doctor or pharmacist before use if you are now taking a prescription drug. Antacids may interact with certain prescription drugs.

OTHER SAFETY INFORMATION

Do not take more than 5 chews in a 24-hour period, or use the maximum dosage for more than 2 weeks, except under the advice and supervision of a physician.

Each chew contains: calcium 300 mg, magnesium 1 mg

Contains soy

PREGNANCY OR BREAST FEEDING

If pregnant or breast-feeding, ask a health professional before use.

Keep out of reach of children.

Directions

Adults and children 12 years and older chew and swallow 1 to 2 chews every 2-4 hours as needed. Do not exceed 5 chews in 24 hours. Children under 12 years consult a doctor.

INACTIVE INGREDIENT

Inactive ingredients: Beeswax, carmine, carnauba wax, citric acid, corn syrup, DL-alpha tocopherol, ethyl acetate, FD&C blue no. 1 aluminum lake, FD&C red no. 40 aluminum lake, FD&C yellow no. 5 lake (tartrazine), FD&C yellow no. 6, FD&C yellow no. 6 aluminum lake, gum arabic, hydrogenated coconut oil, medium chain triglycerides, methyl paraben, modified corn starch, natural and artificial flavors, pregelatinized corn starch, propylene glycol, propyl paraben, phosphoric acid, purified water, shellic, sodium benzoate, sorbic acid, sorbitol, soy lecithin, soybean oil, sucrose, and titanium dioxide.

QUESTIONS

Questions? Or to report an adverse event call 1-800-245-2898 Monday - Friday, 9AM to 4PM EST